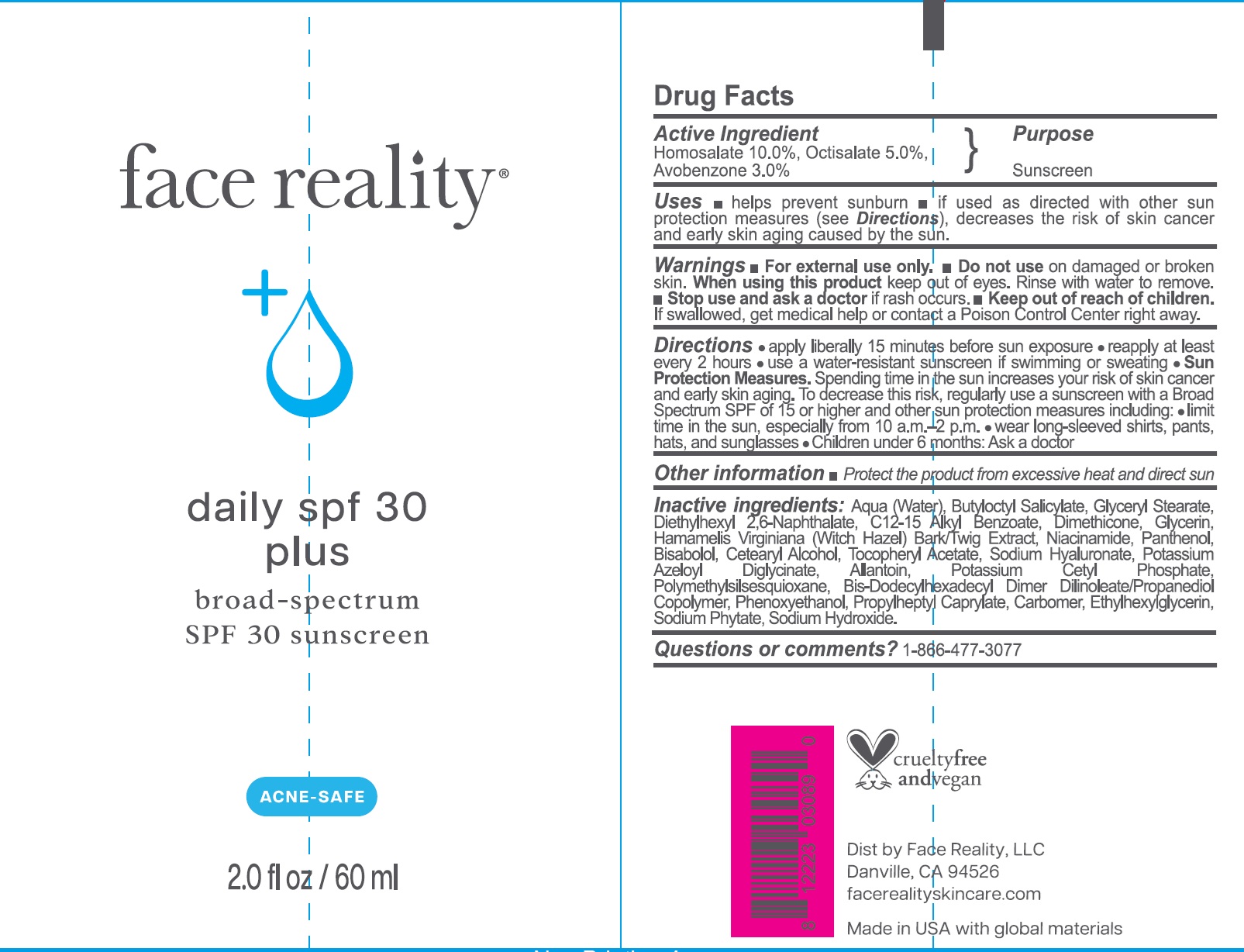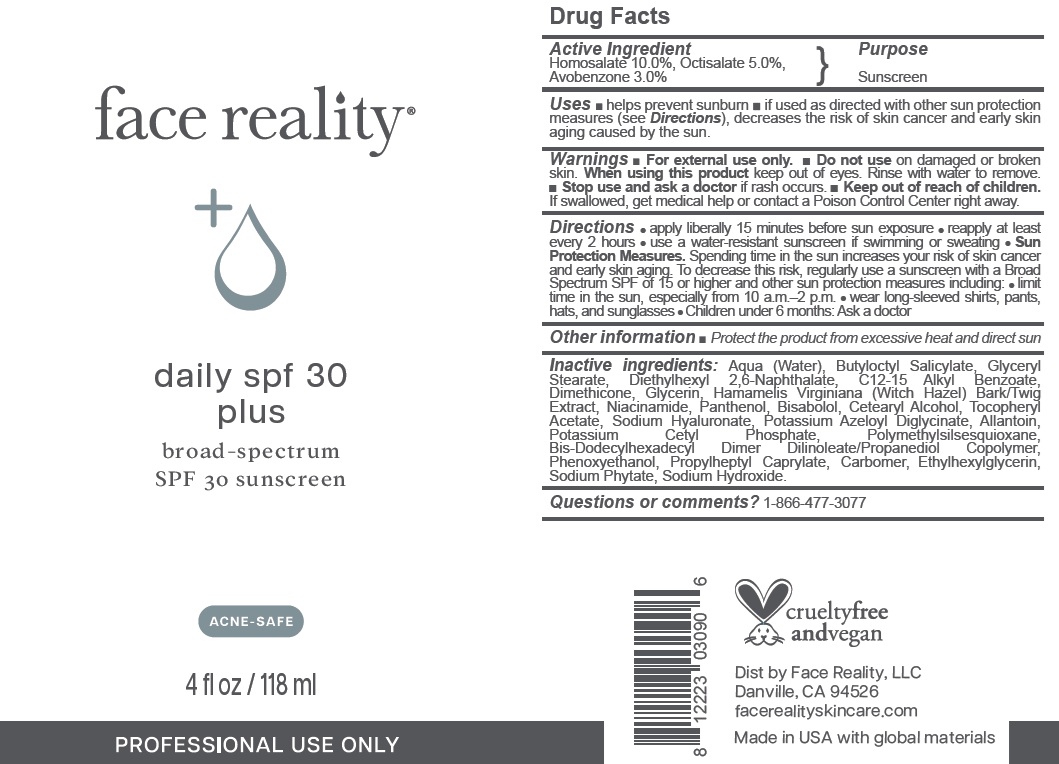 DRUG LABEL: Face Reality daily spf 30 plus Sunscreen SPF 30
NDC: 70707-453 | Form: CREAM
Manufacturer: Face Reality, LLC
Category: otc | Type: HUMAN OTC DRUG LABEL
Date: 20241220

ACTIVE INGREDIENTS: HOMOSALATE 100 mg/1 mL; OCTISALATE 50 mg/1 mL; AVOBENZONE 30 mg/1 mL
INACTIVE INGREDIENTS: WATER; BUTYLOCTYL SALICYLATE; GLYCERYL MONOSTEARATE; DIETHYLHEXYL 2,6-NAPHTHALATE; ALKYL (C12-15) BENZOATE; DIMETHICONE; GLYCERIN; HAMAMELIS VIRGINIANA BARK; NIACINAMIDE; PANTHENOL; BISABOLOL; CETOSTEARYL ALCOHOL; .ALPHA.-TOCOPHEROL ACETATE; SODIUM HYALURONATE; POTASSIUM AZELOYL DIGLYCINATE; ALLANTOIN; POTASSIUM CETYL PHOSPHATE; POLYMETHYLSILSESQUIOXANE (4.5 MICRONS); PHENOXYETHANOL; PROPYLHEPTYL CAPRYLATE; CARBOMER HOMOPOLYMER, UNSPECIFIED TYPE; ETHYLHEXYLGLYCERIN; PHYTATE SODIUM; SODIUM HYDROXIDE

Face Reality daily spf 30 plus Sunscreen SPF 30

Active Ingredient

Homosalate 10.0%, Octisalate 5.0%, Avobenzone 3.0%

Purpose

Sunscreen

Uses

- helps prevent sunburn
- if used as directed with other sun protection measures (see Directions), decreases the risk of skin cancer and early skin aging caused by the sun.

Warnings

For external use only.

Do not use

- on damaged or broken skin.

When using this product

keep out of eyes. Rinse with water to remove.

Stop use and ask a doctor

- if rash occurs.

Keep out of reach of children.

- If swallowed, get medical help or contact a Poison Control Center right away.

Directions

- apply liberally 15 minutes before sun exposure
- reapply at least every 2 hours
- use a water-resistant sunscreen if swimming or sweating
- Sun Protection Measures.Spending time in the sun increases your risk of skin cancer and early skin aging. To decrease this risk, regularly use a sunscreen with a Broad Spectrum SPF of 15 or higher and other sun protection measures including:
- limit time in the sun, especially from 10 a.m.-2 p.m.
- wear long-sleeved shirts, pants, hats, and sunglasses
- Children under 6 months: Ask a doctor

Other information

- Protect the product from excessive heat and direct sun

Inactive ingredients:

Aqua (Water), Butyloctyl Salicylate, Glyceryl Stearate, Diethylhexyl 2,6-Naphthalate, C12-15 Alkyl Benzoate, Dimethicone, Glycerin, Hamamelis Virginiana (Witch Hazel) Bark/Twig Extract, Niacinamide, Panthenol, Bisabolol, Cetearyl Alcohol, Tocopheryl Acetate, Sodium Hyaluronate, Potassium Azeloyl Diglycinate, Allantoin, Potassium Cetyl Phosphate, Polymethylsilsesquioxane, Bis-Dodecylhexadecyl Dimer Dilinoleate/Propanediol Copolymer, Phenoxyethanol, Propylheptyl Caprylate, Carbomer, Ethylhexylglycerin, Sodium Phytate, Sodium Hydroxide.

Questions or comments?

1-866-477-3077